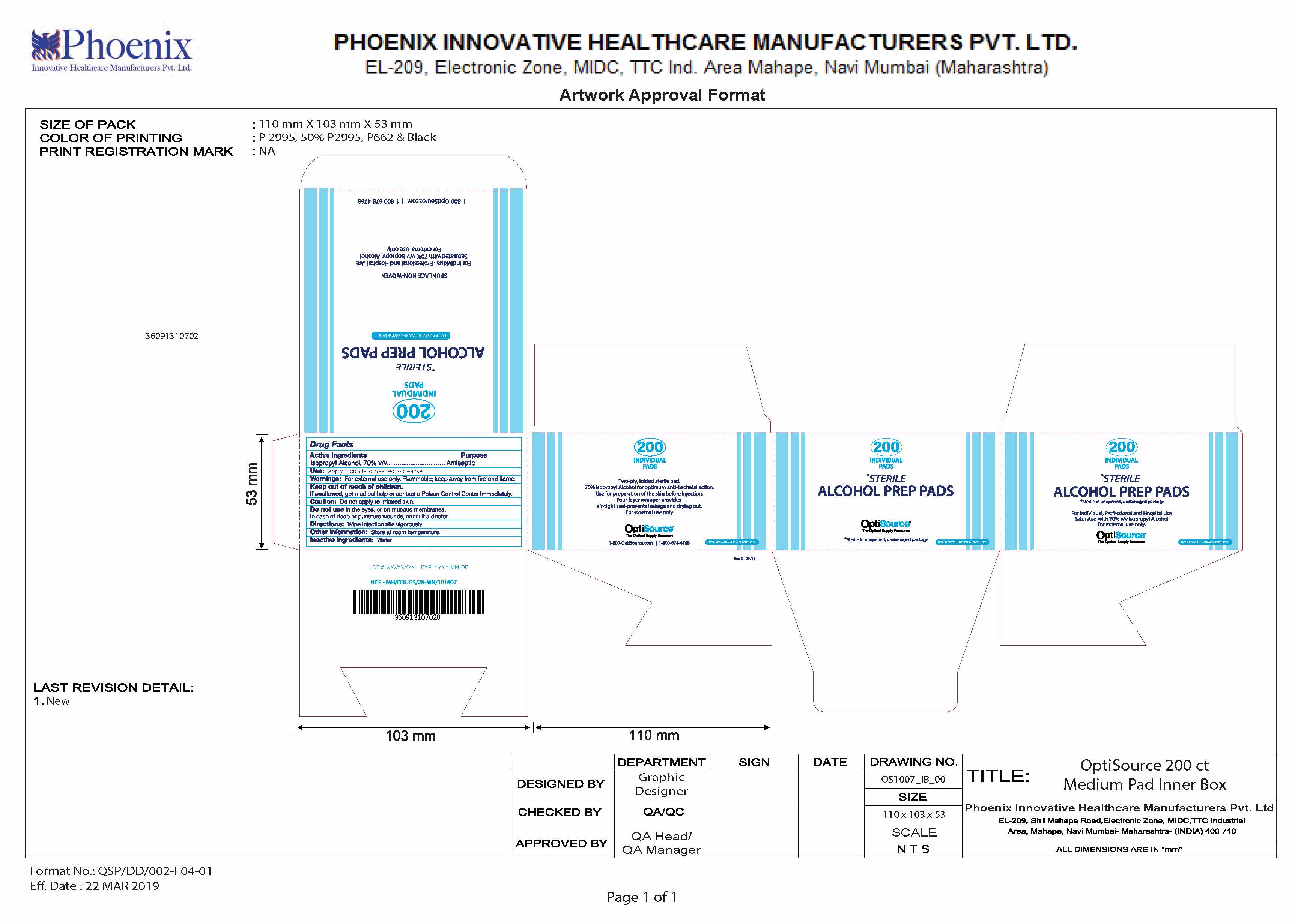 DRUG LABEL: Alcohol Prep Pads
NDC: 60913-107 | Form: SWAB
Manufacturer: Phoenix Healthcare Solutions LLC
Category: otc | Type: HUMAN OTC DRUG LABEL
Date: 20251023

ACTIVE INGREDIENTS: ISOPROPYL ALCOHOL 70 mL/100 mL
INACTIVE INGREDIENTS: WATER

OptiSource Alcohol Prep Pad

ACTIVE INGREDIENT

Isopropyl Alcohol 70% v/v

PURPOSE

Antiseptic

INDICATIONS AND USAGE

Apply topically as needed to cleanse

WARNINGS

For external use only. Flammable; keep away from fire and flame.

KEEP OUT OF REACH OF CHILDREN

If swallowed, get medical help or contact a Poison Control Center immediately.

OTHER SAFETY INFORMATION

Do not apply to irritated skin.

DO NOT USE

In the eyes, or on mucous membranes. In case of deep or puncture wounds, consult a doctor.

DOSAGE AND ADMINISTRATION

Wipe injection site vigorously.

STORAGE AND HANDLING

Store at room temperature.

INACTIVE INGREDIENT

Water